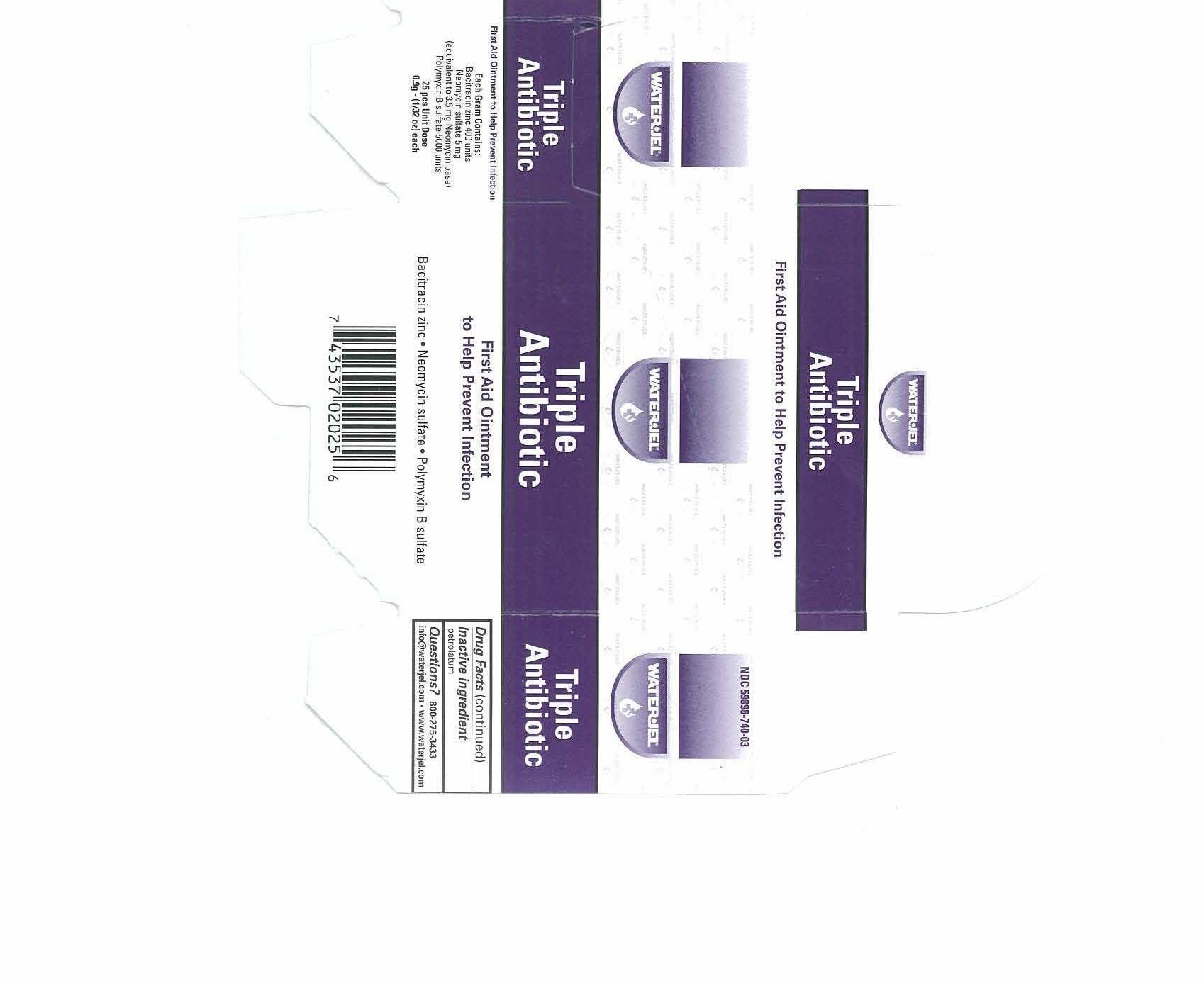 DRUG LABEL: Water-Jel 3-in-1 Antibiotic
NDC: 59898-740 | Form: OINTMENT
Manufacturer: Water-Jel Technologies
Category: otc | Type: HUMAN OTC DRUG LABEL
Date: 20171116

ACTIVE INGREDIENTS: BACITRACIN ZINC 417.8 [iU]/1 g; POLYMYXIN B SULFATE 5322.8 [iU]/1 g; NEOMYCIN SULFATE 3.5 mg/1 g
INACTIVE INGREDIENTS: PETROLATUM

Triple Antibiotic Ointment

Active ingredients (each gram contains)

Bacitracin zinc 400 units

Neomycin sulfate (5 mg equivalent to 3.5 mg Neomycin base)

Polymyxin B sulfate 5000 units

Purpose

First aid antibiotic

First aid antibiotic

First aid antibiotic

Uses

first aid to help prevent infection in

- minor cuts
- scrapes
- burns

Warnings

For external use only

Do not use

- in the eyes or over large areas of the body
- if you are allergic to any of the ingredients
- longer than 1 week unless directed by a doctor

Ask a doctor before use if you have

- a deep or puncture wounds, animal bites, or serious burns

Keep out of the reach of children

If swallowed, get medical help or contact a Poison Control Center right away.

Directions

- clean the affected area
- apply a small amount of product (an amount equal to the surface area of the tip of a finger) on the area 1 to 3 times daily
- may be covered with a sterile bandage

Other information

- store at 15o to 25oC (59o to 77oF)
- tamper evident sealed packets
- do not use any opened or torn packets
- you may report a serious adverse reaction to this product to 800 275-3433

Inactive ingredient

petrolatum

Questions or comments?

800-275-3433

info@waterjel.com www.waterjel.com

Principal Display Panel

Enter section text here